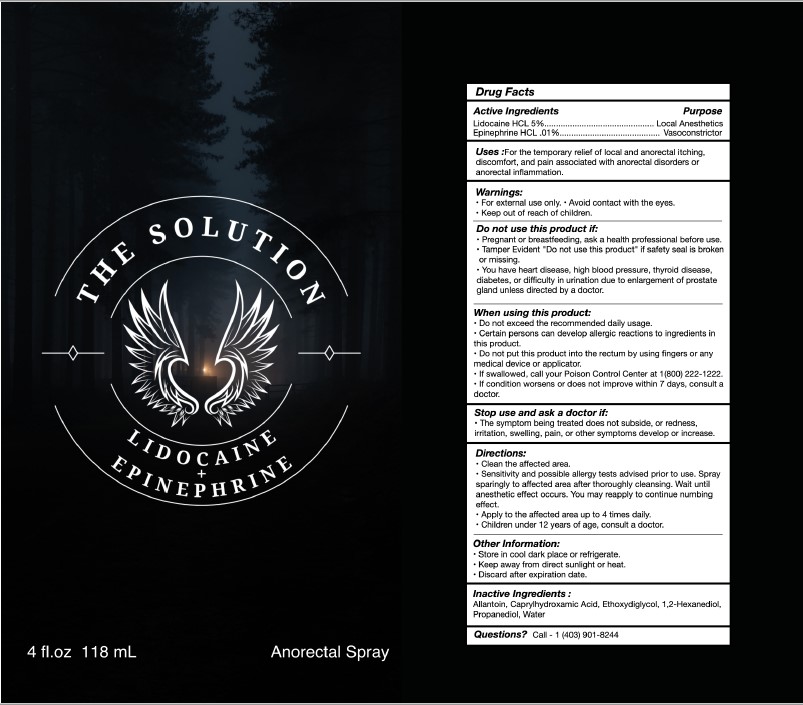 DRUG LABEL: THE SOLUTION
NDC: 82617-101 | Form: SPRAY
Manufacturer: SCALP TECH INC
Category: otc | Type: HUMAN OTC DRUG LABEL
Date: 20250108

ACTIVE INGREDIENTS: LIDOCAINE HYDROCHLORIDE 5 g/100 mL; EPINEPHRINE HYDROCHLORIDE 0.01 g/100 mL
INACTIVE INGREDIENTS: CAPRYLHYDROXAMIC ACID; DIETHYLENE GLYCOL MONOETHYL ETHER; WATER; ALLANTOIN; PROPANEDIOL; 1,2-HEXANEDIOL

SCALP TECH (as PLD) - THE SOLUTION (82617-101)

ACTIVE INGREDIENTS

LIDOCAINE HCL 5%

EPINEPHRINE HCL .01%

PURPOSE

LOCAL ANESTHETICS

VASOCONSTRICTOR

USES

FOR THE TEMPORARY RELIEF OF LOCAL AND ANORECTAL ITCHING, DISCOMFORT, AND PAIN ASSOCIATED WITH ANORECTAL DISORDERS OR ANORECTAL INFLAMMATION.

WARNINGS

- FOR EXTERNAL USE ONLY.
- AVOID CONTACT WITH THE EYES.

KEEP OUT OF REACH OF CHILDREN.

DO NOT USE THIS PRODUCT IF:

- PREGNANT OR BREASTFEEDING, ASK A HEALTH PROFESSIONAL BEFOR EUSE.
- TAMPER EVIDENT "DO NOT USE THIS PRODUCT" IF SAFETY SEAL IS BROKEN OR MISSING.
- YOU HAVE A HEART CONDITION, HIGH BLOOD PRESSURE, THYROID DISEASE, DIABETES, OR DIFFICULTY IN URINATION DUE TO ENLARGEMENT OF PROSTATE GLAND UNLESS DIRECTED BY A DOCTOR.

WHEN USING THIS PRODUCT:

- DO NOT EXCEED THE RECOMMENDED DAILY USAGE.
- CERTAIN PERSONS CAN DEVELOP ALLERGIC REACTIONS TO INGREDIENTS IN THIS PRODUCT.
- DO NOT PUT THIS PRODUCT INTO THE RECTUM BY USING FINGERS OR ANY MEDICAL DEVICE OR APPLICATOR.
- IF SWALLOWED, CALL YOUR POISON CONTROL CENTER AT 1(800)222-1222.
- IF CONDITION WORSENS OR DOES NOT IMPROVE WITHIN 7 DAYS, CONSULT A DOCTOR.

STOP USE AND ASK A DOCTOR IF:

- THE SYMPTOM BEING TREATED DOES NOT SUBSIDE, OR REDNESS, IRRITATION, SWELLING, PAIN, OR OTHER SYMPTOMS DEVELOP OR INCREASE.

DIRECTIONS

- CLEAN THE AFFECTED AREA.
- SENSITIVITY AND POSSIBLE ALLERGY TESTS ADVISED PRIOR TO USE. SPRAY SPARINGLY TO AFFECTED AREA AFTER THOROUGHLY CLEANSING. WAIT UNTIL ANESTHETIC EFFECT OCCURS. YOU MAY REAPPLY TO CONTINUE NUMBING AFFECT.
- APPLY TO THE AFFECTED AREA UP TO 4 TIMES DAILY.
- CHILDREN UNDER 12 YEARS OF AGE, CONSULT A DOCTOR.

OTHER INFORMATION

- STORE IN COOL DARK PLACE OR REFRIGERATE.
- KEEP AWAY FROM DIRECT SUNLIGHT OR HEAT.
- DISCARD AFTER EXPIRATION DATE.

INACTIVE INGREDIENTS

ALLANTOIN, CAPRYLHYDOXAMIC ACID, ETHOXYDIGLYCOL, 1,2-HEXANEDIOL, PROPANEDIOL, WATER

QUESTIONS?

CALL - 1 (403) 901-8244